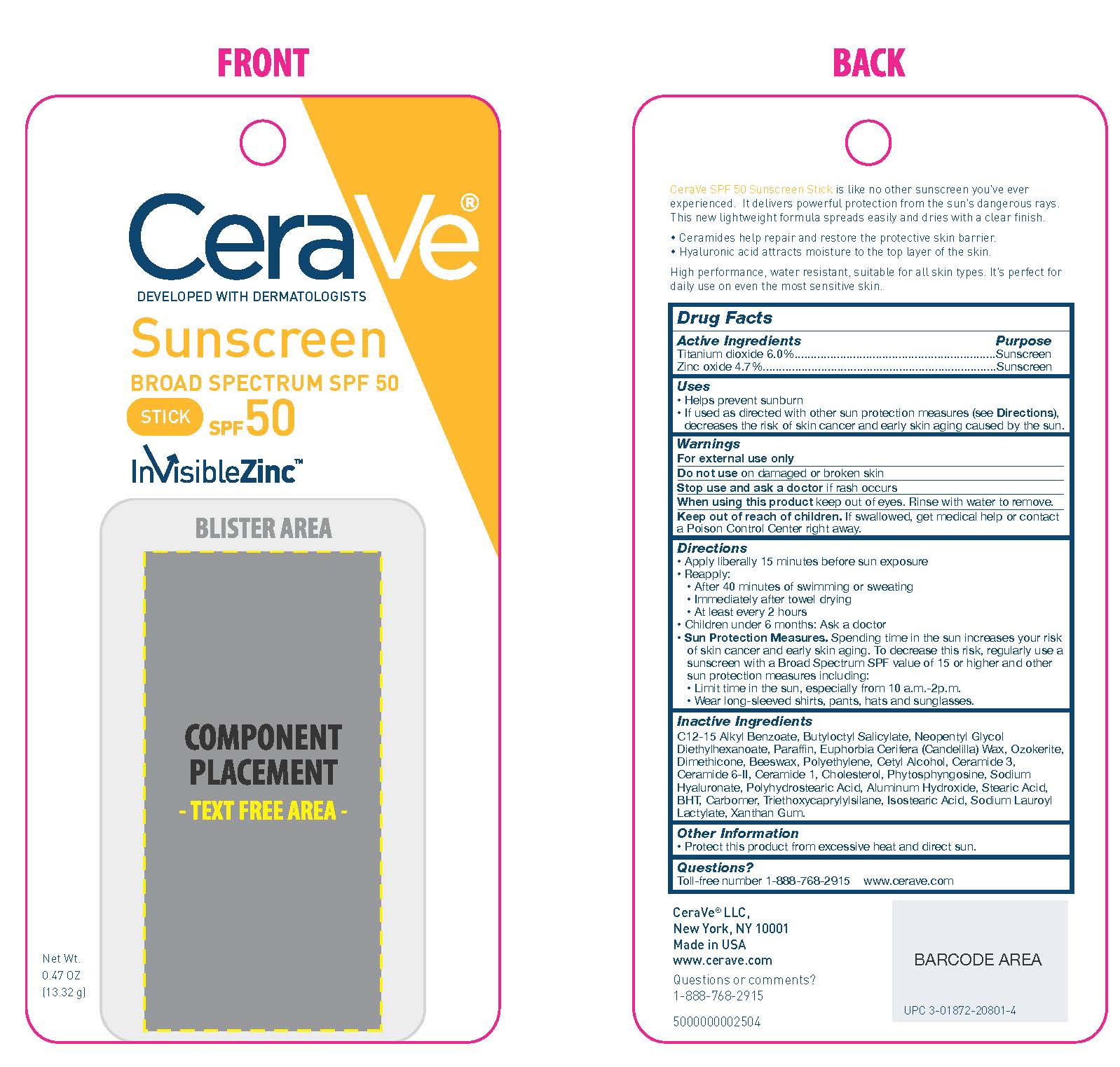 DRUG LABEL: CeraVe Developed with Dermatologists Sunscreen Broad Spectrum SPF 50
NDC: 49967-014 | Form: STICK
Manufacturer: L'Oreal USA Products Inc
Category: otc | Type: HUMAN OTC DRUG LABEL
Date: 20231231

ACTIVE INGREDIENTS: Titanium Dioxide 0.80 g/13.32 g; Zinc Oxide 0.63 g/13.32 g
INACTIVE INGREDIENTS: ALKYL (C12-15) BENZOATE; BUTYLOCTYL SALICYLATE; NEOPENTYL GLYCOL DIETHYLHEXANOATE; PARAFFIN; CANDELILLA WAX; CERESIN; DIMETHICONE; YELLOW WAX; HIGH DENSITY POLYETHYLENE; CETYL ALCOHOL; CERAMIDE NP; CERAMIDE AP; CERAMIDE 1; CHOLESTEROL; PHYTOSPHINGOSINE; HYALURONATE SODIUM; POLYHYDROXYSTEARIC ACID (2300 MW); ALUMINUM HYDROXIDE; STEARIC ACID; BUTYLATED HYDROXYTOLUENE; TRIETHOXYCAPRYLYLSILANE; ISOSTEARIC ACID; SODIUM LAUROYL LACTYLATE; XANTHAN GUM

Drug Facts

Active ingredients

Titanium dioxide 6%

Zinc oxide 4.7%

Purpose

Sunscreen

Uses

- helps prevent sunburn
- if used as directed with other sun protection measures (see Directions), decreases the risk of skin cancer and early skin aging caused by the sun

Warnings

For external use only

Do not use

on damaged or broken skin

Stop use and ask a doctor if

rash occurs

When using this product

keep out of eyes. Rinse with water to remove.

Keep out of reach of children.

If swallowed, get medical help or contact a Poison Control Center right away.

Directions

- apply liberally 15 minutes before sun exposure
- reapply:
- after 40 minutes of swimming or sweating
- immediately after towel drying
- at least every 2 hours
- children under 6 months of age: Ask a doctor
- Sun Protection Measures. Spending time in the sun increases your risk of skin cancer and early skin aging. To decrease this risk, regularly use a sunscreen with a Broad Spectrum SPF value of 15 or higher and other sun protection measures including: • limit time in the sun, especially from 10 a.m.-2 p.m.•wear long-sleeved shirts, pants, hats and sunglasses

Inactive Ingredients

C12-15 Alkyl Benzoate, Butyloctyl Salicylate, Neopentyl Glycol Diethylhexanoate, Paraffin, Euphobia Cerifera (Candelilla) Wax, Ozokerite, Dimethicone, Beeswax, Polyethylene, Cetyl Alcohol, Ceramide 3, Ceramide 6-II, Ceramide 1, Cholesterol, Phytosphingosine, Sodium Hyaluronate, Polyhydrostearic Acid, Aluminum Hydroxide, Stearic Acid, BHT, Carbomer, Triethoxycaprylylsilane, Isostearic Acid, Sodium Lauroyl Lactylate, Xanthan Gum

Other information

Protect this product from excessive heat and direct sun

Questions?

Toll-free number 1-888-768-2915
www.cerave.com